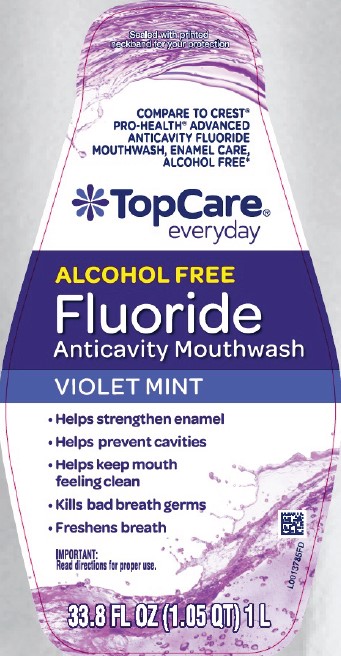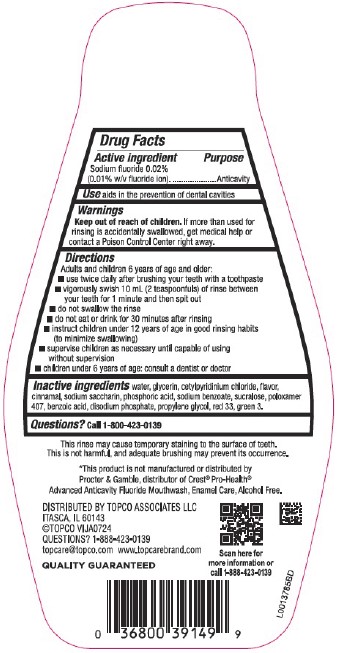 DRUG LABEL: Alcohol-Free Anticavity
NDC: 36800-482 | Form: LIQUID
Manufacturer: Topco Associates LLC
Category: otc | Type: HUMAN OTC DRUG LABEL
Date: 20260213

ACTIVE INGREDIENTS: SODIUM FLUORIDE 0.1 mg/1 mL
INACTIVE INGREDIENTS: WATER; GLYCERIN; CETYLPYRIDINIUM CHLORIDE; CINNAMALDEHYDE; SACCHARIN SODIUM; PHOSPHORIC ACID; SODIUM BENZOATE; SUCRALOSE; POLOXAMER 407; BENZOIC ACID; SODIUM PHOSPHATE, DIBASIC, ANHYDROUS; PROPYLENE GLYCOL; D&C RED NO. 33; FD&C GREEN NO. 3

Top Care 482.002/482AC
Alcohol Free Fluoride Violet Mint Mouthwash

Active ingredient

Sodium fluoride 0.02% (0.01% w/v fluoride ion)

Purpose

Anticavity

Use

aids in the prevention of dental cavities

Warnings

For this product

Keep out of reach of children.

If more than used for rinsing is accidentally swallowed, get medical help or contact a Poison Control Center right away.

Directions

Adults and children 6 years of age and older:

- use twice daily after brushing your teeth with a toothpaste
- vigorously swish 10 mL (2 teaspoonfuls) of rinse between your teeth for 1 minute then spit out
- do not swallow the rinse
- do not eat or drink for 30 minutes after rinsing
- instruct children under 12 years of age in good rinsing habits (to minimize swallowing)
- supervise children as necessary until capable of using without supervision
- children under 6 years of age: consult a dentist or doctor

Inactive ingredients

water, glycerin, cetylpyridinium chloride, flavor, cinnamal, sodium saccharin, phosphoric acid, sodium benzoate, sucralose, poloxamer 407, benzoic acid, disodium phosphate, propylene glycol, red 33, green 3

Questions?

Call 1-800-423-0139

Disclaimers

This rinse may cause temporary staining to the surface of teeth.

This is not harmful, and adequate brushing may prevent its occurrence.

*This product is not manufactured or distributed by Procter & Gamble, distributor of Crest®Pro-Health® Advanced Anticavity Fluoride Mouthwash, Enamel Care, Alcohol Free.

Adverse Reaction

DISTRIBUTED BY TOPCO ASSOCIATES LLC

Italsca, IL 60143

©TOPCO VIJA0724

QUESTIONS? 1-888-423-0139

topcare@topco.com www.topcarebrand.com

QUALITY GUARANTEED

Scan here for more information or call 1-888-423-0139

principal display panel

Sealed with printed neckband for your protection

Compare to Crest®Pro-Health®Advanced Anticavity Fluoride Mouthwash, Enamel Care, Alcohol Free*

Topcare®

everyday

Alcohol free Fluoride Anticavity Mouthwash

Violet mint

- Helps strengthen enamel
- Helps prevent cavities
- Helps keep mouth feeling clean
- Kills bad breath germs
- Freshens breath

IMPORTANT: read directions for proper use.

33.8 FL OZ (1.05 QT) 1 L